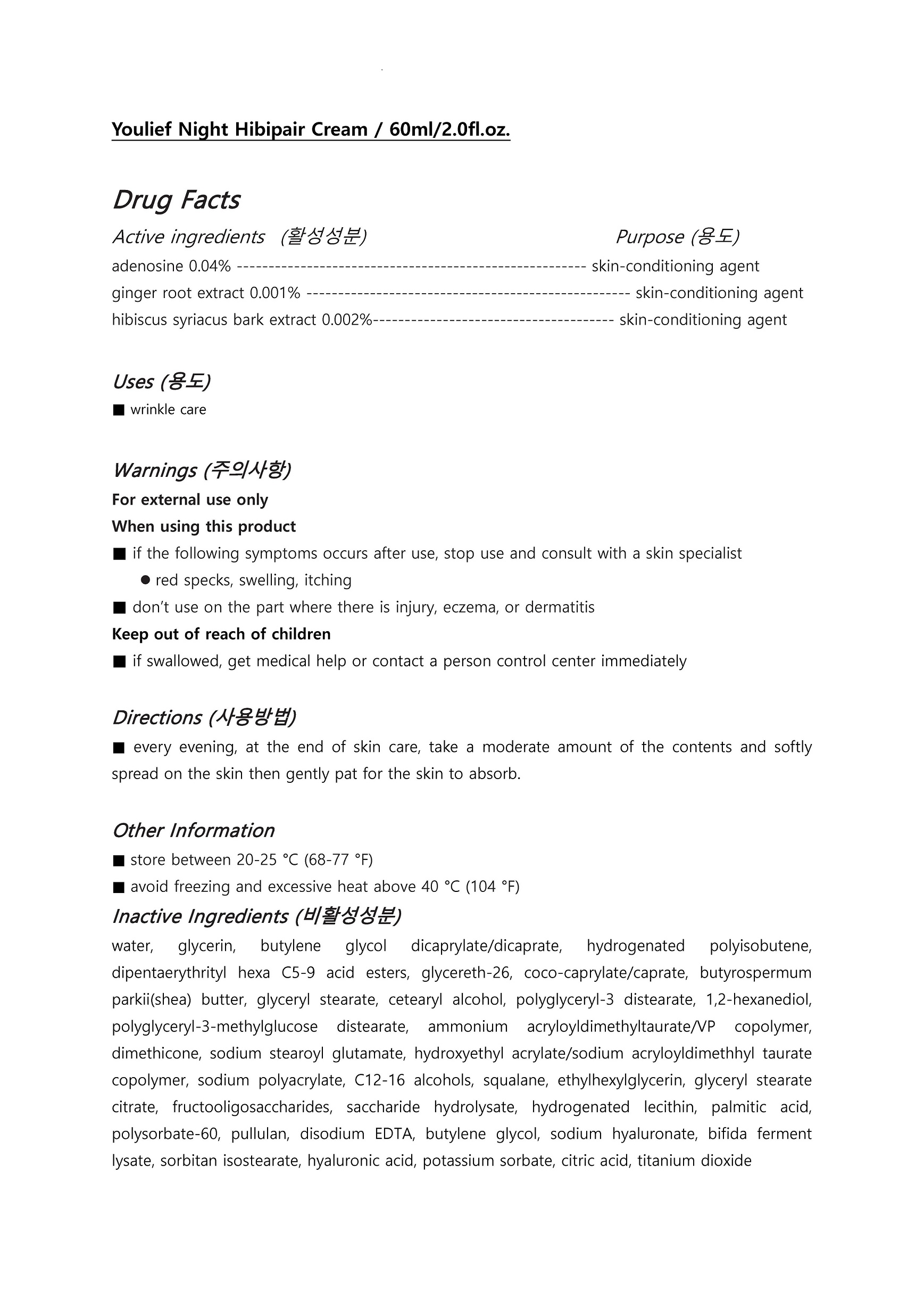 DRUG LABEL: Youlief Night HibipairCream
NDC: 73560-0001 | Form: CREAM
Manufacturer: Plcoskin
Category: otc | Type: HUMAN OTC DRUG LABEL
Date: 20200127

ACTIVE INGREDIENTS: HIBISCUS SYRIACUS BARK 0.002 g/100 mL; ADENOSINE 0.04 g/100 mL; GINGER 0.0001 g/100 mL
INACTIVE INGREDIENTS: WATER; BUTYLENE GLYCOL

Drug Facts

ACTIVE INGREDIENT

Adenosine, ginger root extract, hibiscus syriacus bark extract

INACTIVE INGREDIENT

water, glycerin, butylene glycol dicaprylate/dicaprate, hydrogenated polyisobutene, dipentaerythrityl hexa C5-9 acid esters, glycereth-26, coco-caprylate/caprate, butyrospermum parkii(shea) butter, glyceryl stearate, cetearyl alcohol, polyglyceryl-3 distearate, 1,2-hexanediol, polyglyceryl-3-methylglucose distearate, ammonium acryloyldimethyltaurate/VP copolymer, dimethicone, sodium stearoyl glutamate, hydroxyethyl acrylate/sodium acryloyldimethhyl taurate copolymer, sodium polyacrylate, C12-16 alcohols, squalane, ethylhexylglycerin, glyceryl stearate citrate, fructooligosaccharides, saccharide hydrolysate, hydrogenated lecithin, palmitic acid, polysorbate-60, pullulan, disodium EDTA, butylene glycol, sodium hyaluronate, bifida ferment lysate, sorbitan isostearate, hyaluronic acid, potassium sorbate, citric acid, titanium dioxide

PURPOSE

wrinkle care

keep out of reach of the children

INDICATIONS AND USAGE

every evening, at the end of skin care, take a moderate amount of the contents and softly spread on the skin then gently pat for the skin to absorb.

WARNINGS

For external use only
When using this product

■ if the following symptoms occurs after use, stop use and consult with a skin specialist

red specks, swelling, itching

■ don’t use on the part where there is injury, eczema, or dermatitis

Keep out of reach of children

■ if swallowed, get medical help or contact a person control center immediately

DOSAGE AND ADMINISTRATION

for external use only